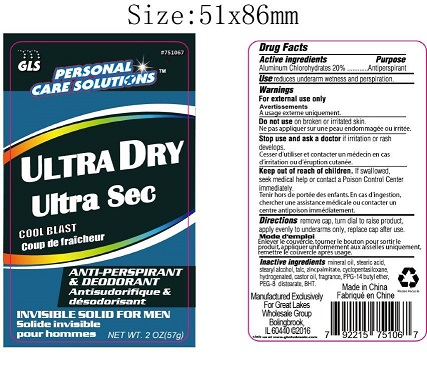 DRUG LABEL: antiperspirant
NDC: 64092-267 | Form: STICK
Manufacturer: Great Lakes Wholesale, Marketing and Sales, Inc.
Category: otc | Type: HUMAN OTC DRUG LABEL
Date: 20160808

ACTIVE INGREDIENTS: ALUMINUM CHLOROHYDRATE 11.4 1/57 g
INACTIVE INGREDIENTS: MINERAL OIL

DESCRIPTION

GLW PERSONAL CARE SOLUTIONS

Ultra Dry cool blast

Anti-perspirant & deodorant

Invisible solid for Men

NET WT. 2 OZ. (57g)

PURPOSE

Reduce underarm wetness and perspiration

Active Ingredients Purpose

Aluminum Chlorohydrates 20%.................................Antiperspirant

PURPOSE

Reduce underarm wetness and perspriation

WARNINGS

For external use only

Do not use on broken or irritated skin

Stop use and ask a doctor if irritation or rash develops.

KEEP OUT OF REACH OF CHILDREN

If swallowed, seek medical help or contact a poison control center immediately.

INSTRUCTIONS FOR USE

Remove cap, turn dial to raise product, apply evenly to underarms only, replace cap after use.

DOSAGE AND ADMINISTRATION

Stick antipirspirant deodorant

20% aluminum chlorohydrates

INDICATIONS AND USAGE

To reduce underarm wetness and perspiration

INACTIVE INGREDIENT

mineral oil, stearic acid, stearyl alcohol, talc, zincpalmitate, cyclopentasiloxane, hydrogenated caster oil, fragrance, PPG-14 butyl ether, PET-8 distearate, BHT